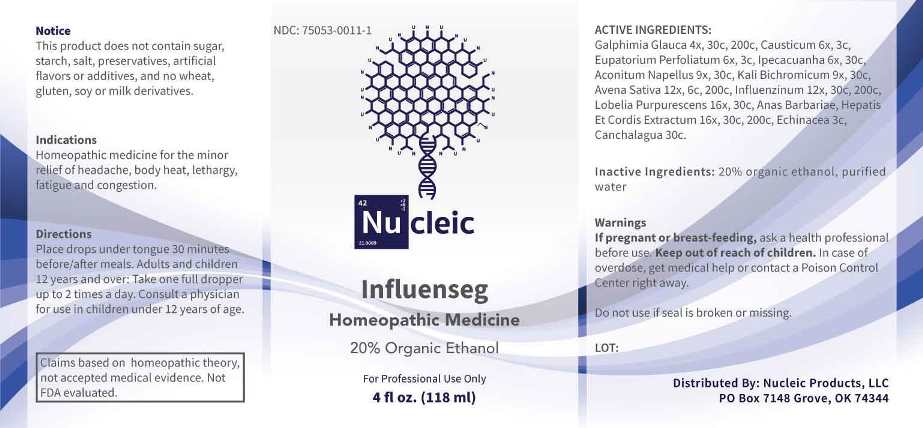 DRUG LABEL: Influenseg
NDC: 75053-0011 | Form: LIQUID
Manufacturer: Nucleic Products, LLC
Category: homeopathic | Type: HUMAN OTC DRUG LABEL
Date: 20251006

ACTIVE INGREDIENTS: GALPHIMIA GLAUCA FLOWERING TOP 4 [hp_X]/1 mL; CAUSTICUM 6 [hp_X]/1 mL; EUPATORIUM PERFOLIATUM FLOWERING TOP 6 [hp_X]/1 mL; IPECAC 6 [hp_X]/1 mL; ACONITUM NAPELLUS WHOLE 9 [hp_X]/1 mL; POTASSIUM DICHROMATE 9 [hp_X]/1 mL; AVENA SATIVA FLOWERING TOP 12 [hp_X]/1 mL; INFLUENZA A VIRUS A/VICTORIA/2570/2019 IVR-215 (H1N1) ANTIGEN (FORMALDEHYDE INACTIVATED) 12 [hp_X]/1 mL; INFLUENZA A VIRUS A/TASMANIA/503/2020 IVR-221 (H3N2) ANTIGEN (FORMALDEHYDE INACTIVATED) 12 [hp_X]/1 mL; INFLUENZA B VIRUS B/WASHINGTON/02/2019 ANTIGEN (FORMALDEHYDE INACTIVATED) 12 [hp_X]/1 mL; INFLUENZA B VIRUS B/PHUKET/3073/2013 ANTIGEN (FORMALDEHYDE INACTIVATED) 12 [hp_X]/1 mL; PRATIA PURPURASCENS 16 [hp_X]/1 mL; CAIRINA MOSCHATA HEART/LIVER AUTOLYSATE 16 [hp_X]/1 mL; ECHINACEA ANGUSTIFOLIA WHOLE 3 [hp_C]/1 mL; ZELTNERA VENUSTA WHOLE FLOWERING 30 [hp_C]/1 mL
INACTIVE INGREDIENTS: WATER; ALCOHOL

Drug Facts:

ACTIVE INGREDIENTS:

Galphimia Glauca 4X, 30C, 200C, Causticum 6X, 3C, Eupatorium Perfoliatum 6X, 3C, Ipecacuanha 6X, 30C, Aconitum Napellus 9X, 30C, Kali Bichromicum 9X, 30C, Avena Sativa 12X, 6C, 200C, Influenzinum (2021-2022) 12X, 30C, 200C, Lobelia Purpurescens 16X, 30C, Anas Barbariae, Hepatis ET Cordis Extractum 16X, 30C, 200C, Echinacea (Angustifolia) 3C, Canchalagua 30C.

INDICATIONS:

Homeopathic medicine for the minor relief of headache, body heat, lethargy, fatigue and congestion.

Claims based on homeopathic theory, not accepted medical evidence. Not FDA evaluated.

WARNINGS:

If pregnant or breast-feeding, ask a health professional before use.

Keep out of reach of children. In case of overdose, get medical help or contact a Poison Control Center right away.

Do not use if seal is broken or missing.

This Product does not contain sugar, starch, salt, preservatives, artificial flavors or additives, and no wheat, gluten, soy or milk derivatives.

Keep out of reach of children. In case of overdose, get medical help or contact a Poison Control Center right away.

DIRECTIONS:

Place drops under tongue 30 minutes before/after meals. Adults and children 12 years and over: Take one full dropper up to 2 times a day. Consult a physician for use in children under 12 years of age.

INDICATIONS:

Homeopathic medicine for the minor relief of headache, body heat, lethargy, fatigue and congestion.

Claims based on homeopathic theory, not accepted medical evidence. Not FDA evaluated.

INACTIVE INGREDIENTS:

20% organic ethanol, purified water

QUESTIONS:

Distributed by:
Nucleic Products, LLC

PO Box 7148 Grove, OK 74344

PACKAGE LABEL DISPLAY:

NDC: 75053-0011-1

Nu cleic

Influenseg

Homeopathic Medicine

For Professional Use Only

4 fl oz. (118 ml)